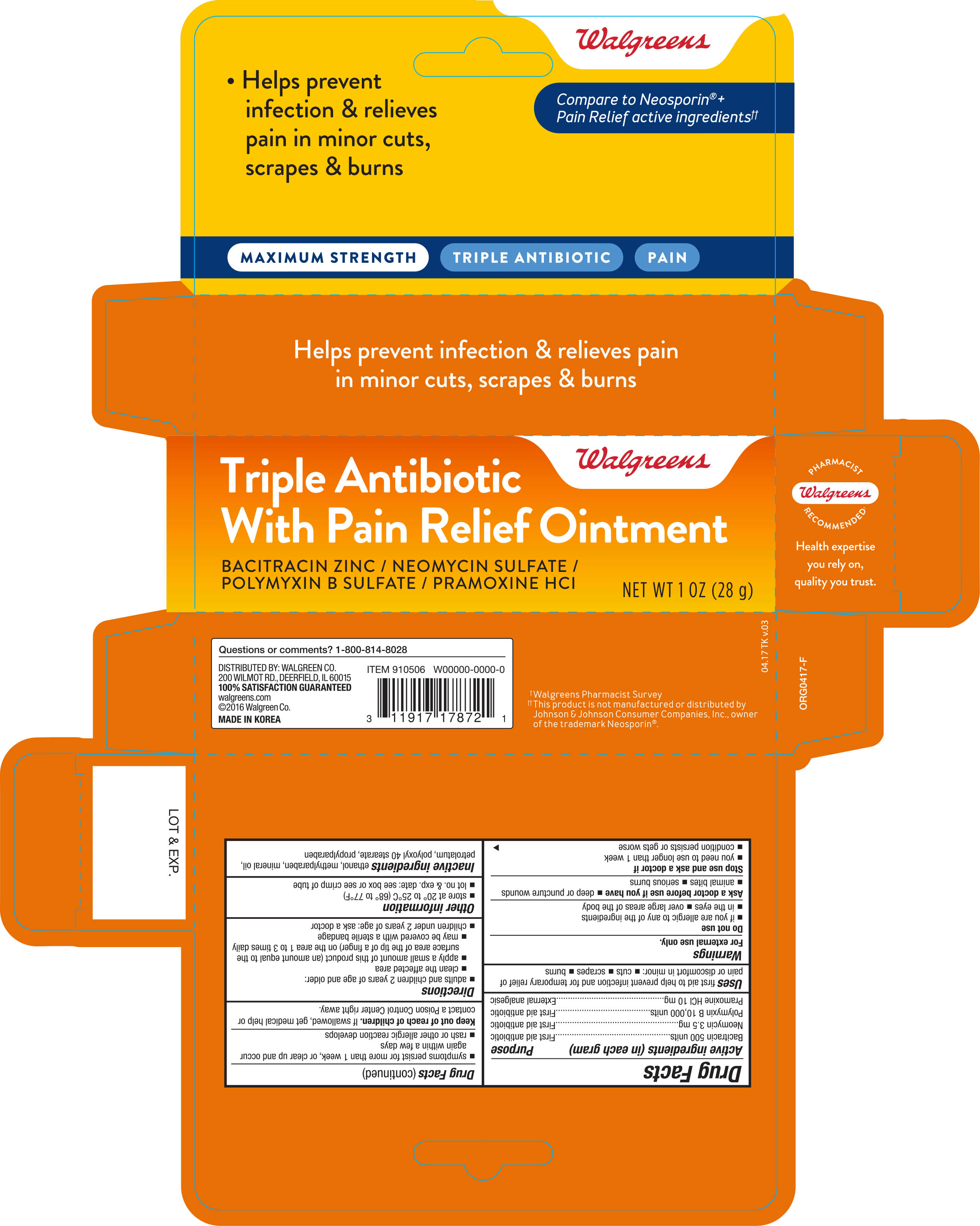 DRUG LABEL: Walgreens Maximum Strength Triple Antibiotic With Pain Relief
NDC: 0363-7872 | Form: OINTMENT
Manufacturer: Walgreen Co.
Category: otc | Type: HUMAN OTC DRUG LABEL
Date: 20180301

ACTIVE INGREDIENTS: BACITRACIN ZINC 500 [USP'U]/1 g; NEOMYCIN SULFATE 3.5 mg/1 g; POLYMYXIN B SULFATE 1000 [USP'U]/1 g; PRAMOXINE HYDROCHLORIDE 10 mg/1 g
INACTIVE INGREDIENTS: ALCOHOL; MINERAL OIL; PARAFFIN; METHYLPARABEN; POLYOXYL 40 STEARATE; PROPYLPARABEN; PETROLATUM

Walgreens Triple Antibiotic Pain Relieving Ointment 1 oz 910506 (2018)

Active ingredients (each gram contains) Purpose

Bacitracin zinc 500 units.................................................................. First aid antibiotic

Neomycin sulfate 3.5 mg.................................................................. First aid antibiotic

Polymyxin B sulfate 10,000 units....................................................... First aid antibiotic

Pramoxine HCI 10 mg...................................................................... External analgesic

Uses

- first aid to help prevent infection and for temporary relief of pain or discomfort due to:
- minor cuts
- scrapes
- burns

Warnings

For external use only

Do not use

- if you are allergic to any of the ingredients
- in the eyes
- over large areas of the body

Ask a doctor before use if you have

- deep or puncture wounds
- animal bites
- serious burns

Stop use and ask a doctor if

- you need to use longer than 1 week
- condition persists or gets worse
- symptoms persist for more than 1 week or clear up and occur again within a few days
- rash or other allergic reaction develops

Keep out of reach of children. If swallowed, get medical help or contact a Poison Control Center right away

Directions

- adults and children 2 years of age and older:
- clean the affected area
- apply a small amount of this product (an amount equal to the surface area of the tip of a finger) on the area 1 to 3 times daily
- may be covered with a sterile bandage
- children under 2 years of age: ask a doctor

Other information

- store at 20°-25°C (68°-77°F)
- Lot No. & Exp. Date: See box or crimp of tube

Inactive ingredients

ethanol, methylparaben, mineral oil, petrolatum, polyoxyl 40 stearate, propylparaben

DOSAGE AND ADMINISTRATION

Distributed by:

Walgreen Co.

200 Wilmot Rd.

Deerfield, IL 60015

Made in Korea